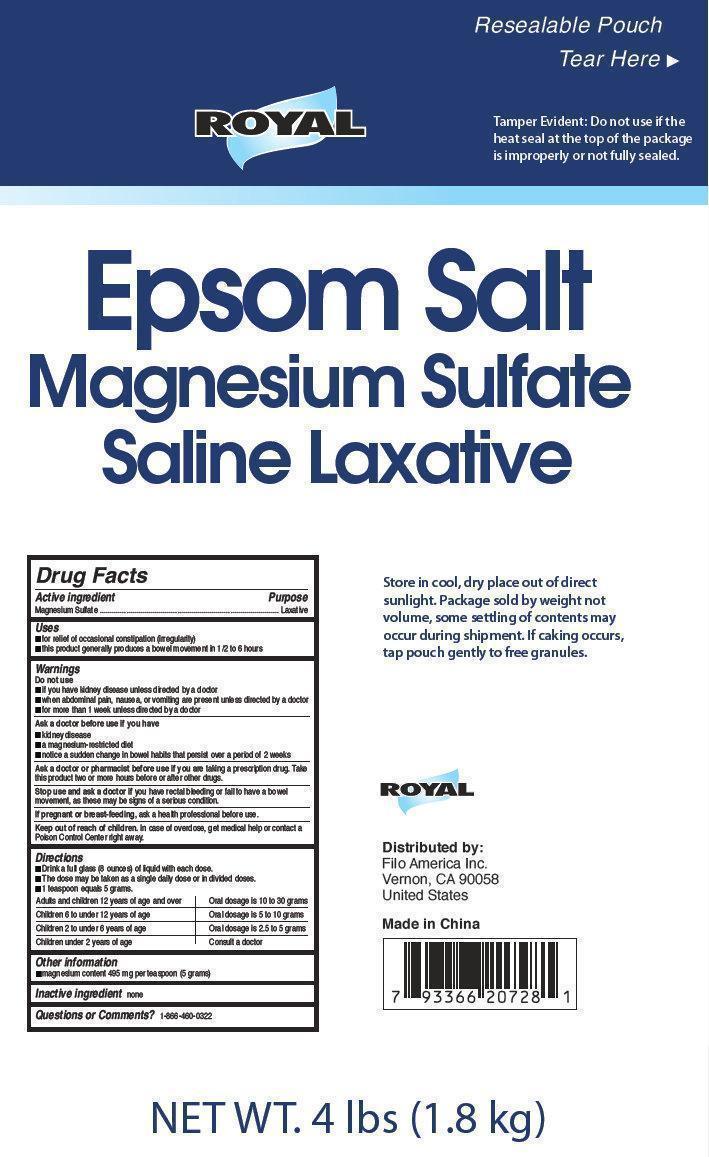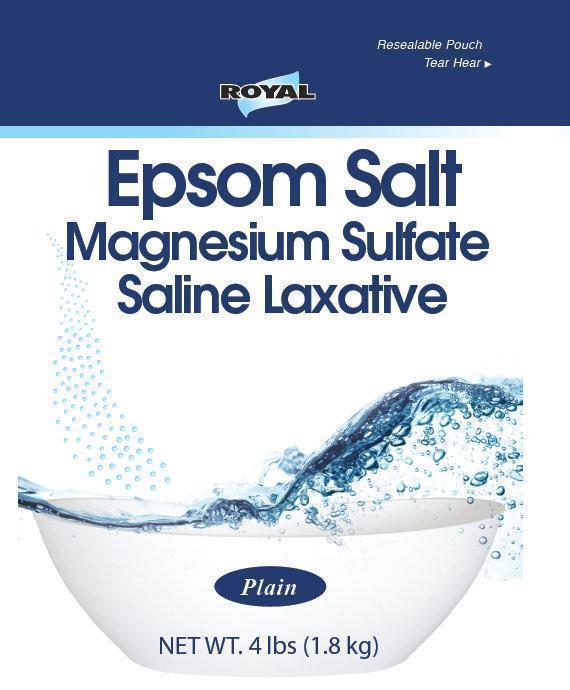 DRUG LABEL: ROYAL Epsom Salt
NDC: 50438-001 | Form: GRANULE, FOR SOLUTION
Manufacturer: Filo America
Category: otc | Type: HUMAN OTC DRUG LABEL
Date: 20260122

ACTIVE INGREDIENTS: MAGNESIUM SULFATE, UNSPECIFIED FORM 1 kg/1 kg

Epsom Salt

OTHER SAFETY INFORMATION

Tamper Evident: Do not use if the heat seal at the top of the package is improperly or not fully sealed.

Active ingredient

Magnesium Sulfate

Purpose

Laxative

Uses

- for relief of occasional constipation (irregularity)
- this product generally produces a bowel movement in 1/2 to 6 hours

Do no use

- if you have kidney disease unless directed by a doctor
- when abdominal pain, nausea, or vomiting are present unless directed by a doctor
- for more than 1 week unless directed by a doctor

Ask a doctor before use if you have

- kidney disease
- a magnesium-restricted diet
- noticed a sudden change in bowel habits that persists over a period of 2 week

Ask a doctor or pharmacist before use if you are

taking a prescription drug. Take this product two or more hours before or after other drugs.

Stop use and ask a doctor if

you have rectal bleeding or failure to have a bowel movement after use. These could be signs of a serious condition.

If pregnant or breast-feeding,

ask a help professional before use.

Keep out of reach of children

In case of overdose, get medical help or contact a Poison Control Center right away.

Directions

Adults and children 12 years and over - Oral dosage is 10 to 30 grams

children 6 to under 12 years of age - Oral dosage is 5 to 10 grams

children 2 to under 6 years of age - Oral dosage is 2.5 to 5 grams

children under 2 years of age - consult a doctor

- Drink a full glass (8 ounces) of liquid with each dose.
- The dose may be taken as a single daily dose or in divided doses.
- 1 teaspoon equals 5 grams.

Other information

- Magnesium content 495 mg per teaspoon (5 grams)

Inactive Ingredients

none

Questions

Questions or comments? 1-800-632-6900

Side panel information

Store in cool, dry place out of direct

sunlight. Package sold by weight not

volume, some settling of contents may

occur during shipment. If caking occurs,

tap pouch gently to free granules.

ROYAL

Distributed by:

Filo America Inc.

Vernon, CA 90058

United States

Made in China

Principal display panel

Royal

Epsom Salt

Magnesium Sulfate

Saline Laxative

Plain

NET WT. 4 lbs (1.8 kg)

Distributed by:

Filo America Inc.

Vernon, CA 90058

United States

Made in China

NET WT. 4 lbs (1.8 kg)